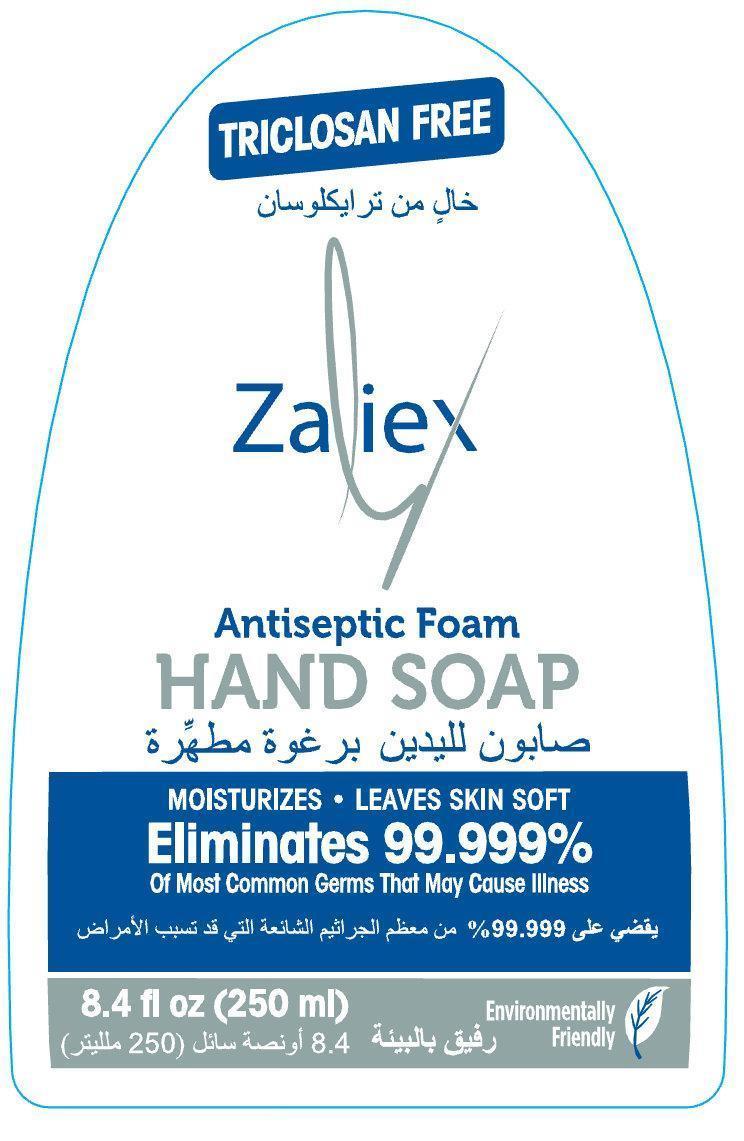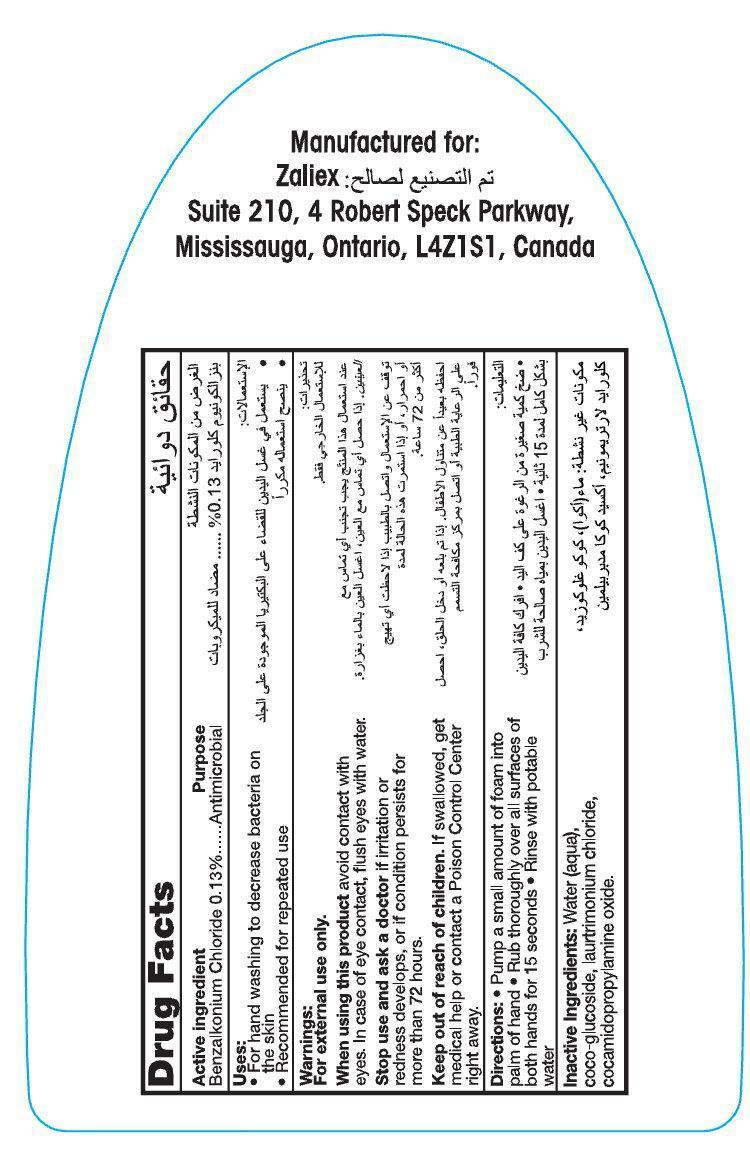 DRUG LABEL: Zaliex Antiseptic Hand
NDC: 76452-002 | Form: SOAP
Manufacturer: SAS Healthcare Inc
Category: otc | Type: HUMAN OTC DRUG LABEL
Date: 20120912

ACTIVE INGREDIENTS: BENZALKONIUM CHLORIDE 0.13 mg/1 mL
INACTIVE INGREDIENTS: WATER; COCO GLUCOSIDE; COCAMIDOPROPYLAMINE OXIDE

Zaliex Antiseptic Foam Hand Soap

Active Ingredient

Benzalkonium Chloride 0.13%

Purpose

Antimicrobial

Uses:

- For hand washing to decrease bacteria on the skin
- Recommended for repeated use

Warnings:

For external use only.

When using this product avoid contact with eyes. In case of eye contact, flush with water.

Stop use and ask a doctor if irritation or redness develops, or if condition persists for more than 72 hours.

Keep out of reach of children. If swallowed, get medical help or contact a Poison Control Center right away.

Directions:

- Pump a small amount of foam into palm of hand
- Run thoroughly over all surfaces of both hands for 15 seconds
- Rinse with potable water

Inactive Ingredients:

Water (aqua), coco-glucoside, laurtrimonium chloride, cocamidopropylamine oxide.

Manufactured for:

Zaliex

Suite 210, 4 Robert Speck Parkway,

Mississauga, Ontario, L4Z1S1, Canada

Zaliex Antiseptic Foam Hand Soap 250ml | Zaliex Antiseptic Foam Hand Soap 550ml (76452-002-01) | Zaliex Antiseptic Foam Hand Soap 1000ml (76452-002-02)

TRICLOSAN FREE
Zaliex
Antiseptic Foam
HAND SOAP
MOISTURIZES * LEAVES SKIN SOFT
Eliminates 99.999%
Of Most Common Germs That May Cause Illness
8.4 fl oz (250 ml)
Environmentally Friendly